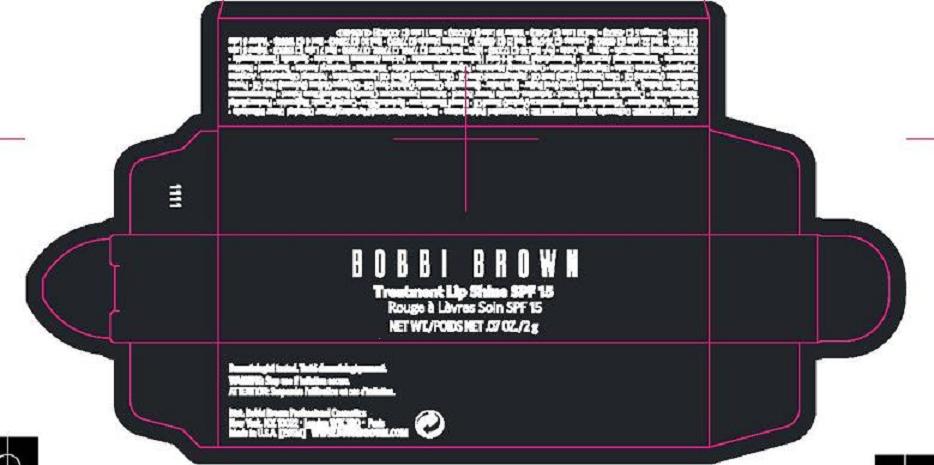 DRUG LABEL: TREATMENT LIPSHINE
NDC: 64141-004 | Form: LIPSTICK
Manufacturer: BOBBI BROWN PROFESSIONAL COSMETICS INC
Category: otc | Type: HUMAN OTC DRUG LABEL
Date: 20100513

ACTIVE INGREDIENTS: OCTINOXATE 7.0 g/100 g

ACTIVE INGREDIENT: TITANIUM DIOXIDE 7.0%

WARNINGS

WARNING: STOP USE IF IRRITATION OCCURS

PACKAGE LABEL

PRINCIPAL DISPLAY PANEL:

BOBBI BROWN

TREATMENT LIPSHINE SPF 15

NET WT/POIDS NET 0.7 OZ./2 g

BOBBI BROWN PROFESSIONAL COSMETICS INC.

NEW YORK, NY 10022